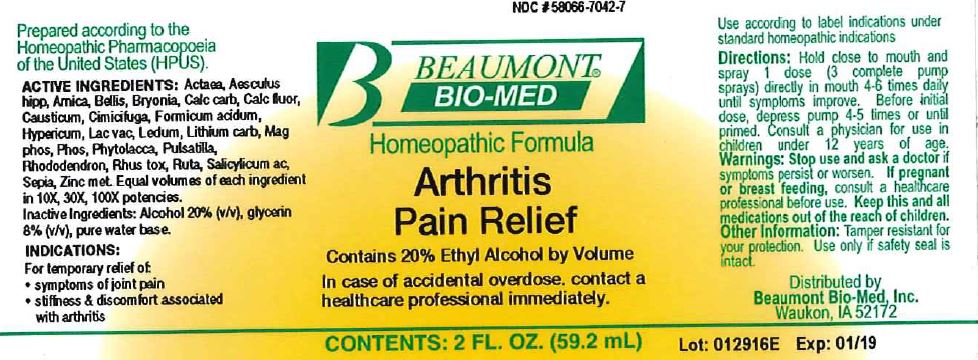 DRUG LABEL: Arthritis Pain Relief
NDC: 58066-7042 | Form: LIQUID
Manufacturer: Beaumont Bio Med
Category: homeopathic | Type: HUMAN OTC DRUG LABEL
Date: 20180101

ACTIVE INGREDIENTS: ACTAEA CIMICIFUGA ROOT 10 [hp_X]/59.2 mL; HORSE CHESTNUT 10 [hp_X]/59.2 mL; ARNICA MONTANA 10 [hp_X]/59.2 mL; BELLIS PERENNIS 10 [hp_X]/59.2 mL; BRYONIA ALBA ROOT 10 [hp_X]/59.2 mL; OYSTER SHELL CALCIUM CARBONATE, CRUDE 10 [hp_X]/59.2 mL; CALCIUM FLUORIDE 10 [hp_X]/59.2 mL; CAUSTICUM 10 [hp_X]/59.2 mL; BLACK COHOSH 10 [hp_X]/59.2 mL; FORMIC ACID 10 [hp_X]/59.2 mL; HYPERICUM PERFORATUM 10 [hp_X]/59.2 mL; COW MILK 10 [hp_X]/59.2 mL; RHODODENDRON TOMENTOSUM LEAFY TWIG 10 [hp_X]/59.2 mL; LITHIUM CARBONATE 10 [hp_X]/59.2 mL; MAGNESIUM PHOSPHATE, DIBASIC TRIHYDRATE 10 [hp_X]/59.2 mL; PHOSPHORUS 10 [hp_X]/59.2 mL; PHYTOLACCA AMERICANA ROOT 10 [hp_X]/59.2 mL; ANEMONE PULSATILLA 10 [hp_X]/59.2 mL; RHODODENDRON AUREUM LEAF 10 [hp_X]/59.2 mL; TOXICODENDRON PUBESCENS LEAF 10 [hp_X]/59.2 mL; RUTA GRAVEOLENS FLOWERING TOP 10 [hp_X]/59.2 mL; SALICYLIC ACID 10 [hp_X]/59.2 mL; SEPIA OFFICINALIS JUICE 10 [hp_X]/59.2 mL; ZINC 10 [hp_X]/59.2 mL
INACTIVE INGREDIENTS: ALCOHOL; GLYCERIN; WATER

Arthritis Pain Relief

ACTIVE INGREDIENT

HPUS active ingredients: Actaea, Aesculus hipp, Arnica, Bellis, Bryonia, Calc carb, Calc fluor, Causticum, Cimicifuga, Formicum acidum, Hypericum, Lac vac, Ledum, Lithium carb, Mag phos, Phos, Phytolacca, Pulsatilla, Rhododendron, Rhus tox, Ruta, Salicylicum ac, Sepia, Zinc met. Equal volumes of each ingredient in 10X, 30X, 100X potencies.

INACTIVE INGREDIENT

Inactive Ingredients: Alcohol @ 20% (v/v), Glycerin @ 8% (v/v), in a pure water base.

INDICATIONS AND USAGE

Indications: For temporary relief of: symptoms of joint pain, Stiffness & discomfort associated with arthritis.

Directions:

- Hold close to mouth and spray 1 dose (3 complete pump sprays) directly in mouth 4-6 times daily until symptoms improve.
- Before initial dose, depress pump 4-5 times or until primed.
- Consult a physician for use in children under 12 years of age.

WARNINGS

Warnings: Stop use and ask a doctor if symptoms persist or worsen. If pregnant or breast feeding, consult a healthcare professional before use. In case of accidental overdose contact a healthcareprofessional immediately.

KEEP OUT OF REACH OF CHILDREN

Keep this and all medications out of the reach of children.

Other information: Tamper resistant for your protection. Use only if safety seal is intact.

PURPOSE

For temporary relief of: symptoms of joint pain, stiffness & discomfort associated with arthritis.